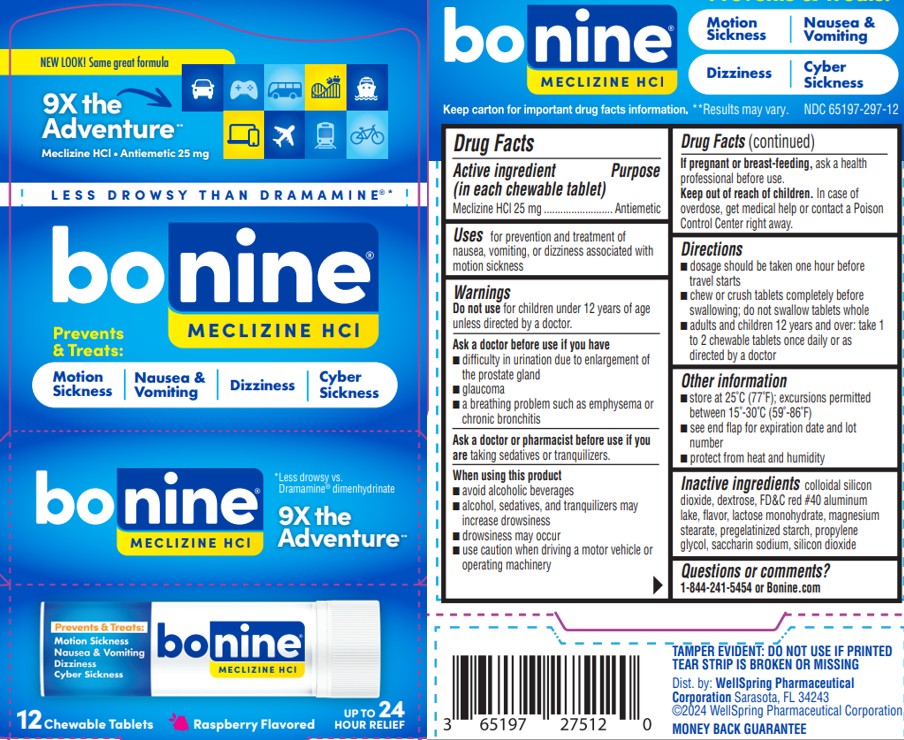 DRUG LABEL: BONINE
NDC: 65197-297 | Form: TABLET, CHEWABLE
Manufacturer: WellSpring Pharmaceutical Corporation
Category: otc | Type: HUMAN OTC DRUG LABEL
Date: 20250321

ACTIVE INGREDIENTS: MECLIZINE HYDROCHLORIDE 25 mg/1 1
INACTIVE INGREDIENTS: LACTOSE MONOHYDRATE; FD&C RED NO. 40; SACCHARIN SODIUM; STARCH, CORN; MAGNESIUM STEARATE; SILICON DIOXIDE

BONINE®
MECLIZINE HYDROCHLORIDE • ANTIEMETIC 25mg
Motion Sickness | Nausea & Vomiting | Dizziness | Cyber Sickness
*Less drowsy vs. Dramamine® dimenhydrinate

Active ingredient (in each tablet)

Meclizine HCl 25 mg

Purpose

Antiemetic

Uses

prevents and treats nausea, vomiting or dizziness associated with motion sickness

Warnings

Do not use

in children under 12 years of age unless directed by a doctor.

Ask a doctor before use if you have

- difficulty in urination due to enlargement of the prostate gland
- glaucoma
- a breathing problem such as emphysema or chronic bronchitis

Ask a doctor or pharmacist before use if you are

taking sedatives or tranquilizers.

When using this product

- avoid alcoholic beverages
- alcohol, sedatives, and tranquilizers may increase drowsiness
- drowsiness may occur
- use caution when driving a motor vehicle or operating machinery

If pregnant or breast-feeding,

ask a health professional before use.

Keep out of reach of children.

In case of overdose, get medical help or contact a Poison Control Center right away.

Directions

- dosage should be taken one hour before travel starts
- chew or crush tablets completely before swallowing; do not swallow tablets whole
- adults and children 12 years and over: take 1 to 2 chewable tablets once daily or as directed by a doctor

Other information

- store at 25˚C (77˚F); excursions permitted between 15˚-30˚C (59˚-86˚F)
- see end flap for expiration date and lot number
- protect from heat and humidity

Inactive ingredients

colloidal silicon dioxide, dextrose, FD&C red #40 aluminum lake, flavor, lactose monohydrate, magnesium stearate, pregelatinized starch, propylene glycol, saccharin sodium, silicon dioxide

Questions or comments?

1 (844) 241-5454 or www.bonine.com

Dist. by:

WellSpring Pharmaceutical
Corporation Sarasota, FL 34243
©2024 WellSpring Pharmaceutical Corporation

TAMPER EVIDENT: DO NOT USE IF PRINTED TEAR STRIP IS BROKEN OR MISSING

MONEY BACK GUARANTEE

PACKAGE LABEL.PRINCIPAL DISPLAY PANEL 65197-297

*Less drowsy vs. Dramamine® dimenhydrinate. Dramamine® is a registered trademark of Medtech Products Inc.

NEW LOOK! Same great formula

9X the Adventure** Meclizine HCl • Antiemetic 25 mg

Bonine 12 ct